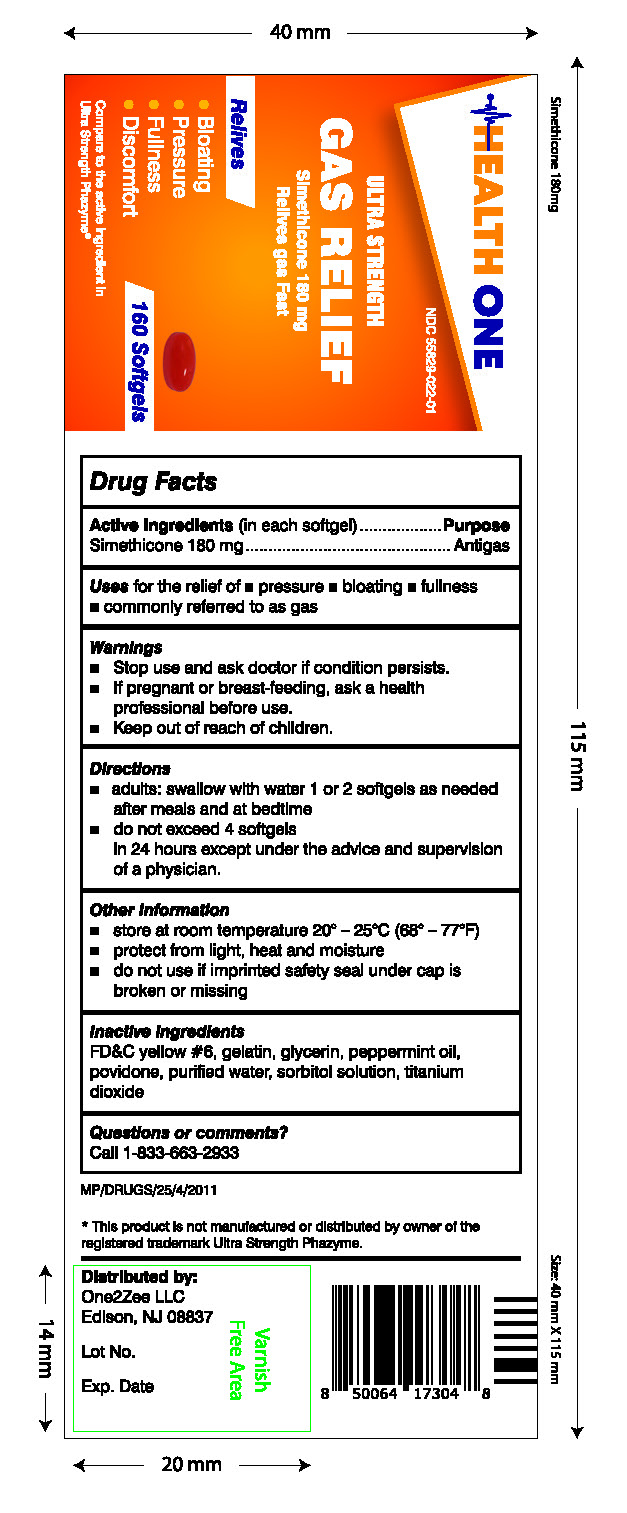 DRUG LABEL: Simethicone 180MG Ultra Strength Gas Relief
NDC: 55629-022 | Form: CAPSULE, LIQUID FILLED
Manufacturer: One2Zee Limited Liability Company
Category: otc | Type: HUMAN OTC DRUG LABEL
Date: 20240924

ACTIVE INGREDIENTS: DIMETHICONE 180 mg/1 1
INACTIVE INGREDIENTS: FD&C YELLOW NO. 6; GELATIN; GLYCERIN; POVIDONE; WATER; SORBITOL SOLUTION; TITANIUM DIOXIDE

Simethicone 180mg Ultra Strength Gas Relief

Active Ingredients (in each softgel)

Simethicone 180 mg

Purpose

Antigas

INDICATIONS AND USAGE

Use for the relief of

- pressure
- bloating
- fullness
- commonly referred to as gas

Warning

- Stop use and ask doctor if condition persists.
- If pregnant or breast-feeding, ask a health professional before use.

Directions

- adults:swallow with water 1 or 2 softgels as needed after meals and at bedtime
- do not exceed 4 softgels in 24 hours except under the advice and supervision of a physician

Other Information

- store at controlled room temperature 20°-25°C (68°-77°F)
- protact from light, heat and moisture
- do not use if imprinted safety seal under cap is broken or missing

INACTIVE INGREDIENT

D&C yellow #6, gelatin, glycerin, povidone, purified water, sorbitol solution, titanium dioxide

Questions or comments?
Call 1-833-663-2933